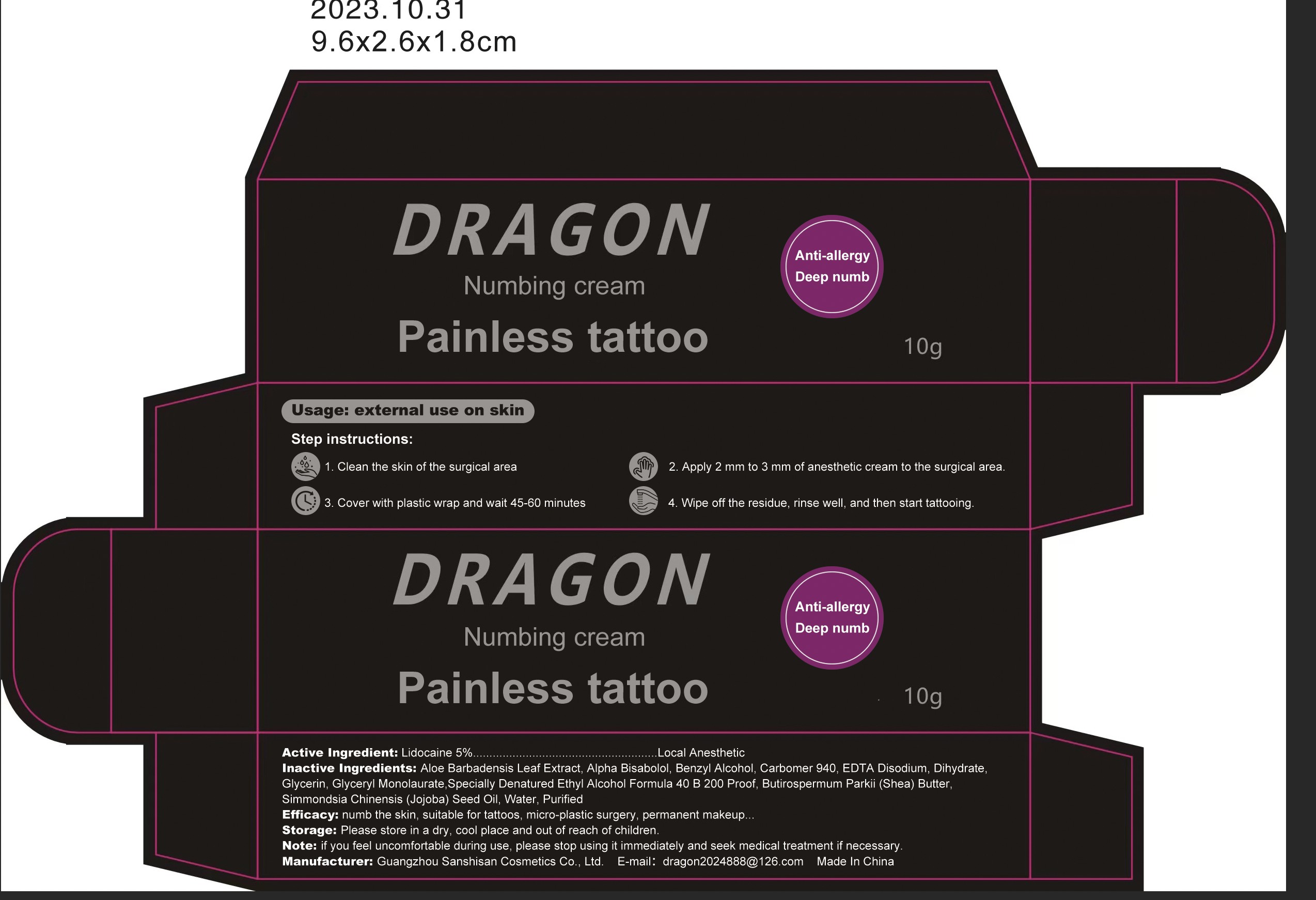 DRUG LABEL: Tattoo numbing cream
NDC: 85342-001 | Form: PASTE
Manufacturer: Guangzhou Sanshisan Cosmetics Co., Ltd.
Category: otc | Type: HUMAN OTC DRUG LABEL
Date: 20250320

ACTIVE INGREDIENTS: LIDOCAINE 50 mg/10 g
INACTIVE INGREDIENTS: BENZYL ALCOHOL; EDETATE DISODIUM; ALOE BARBADENSIS LEAF; TERT-BUTYL ALCOHOL; KUS-121 DIHYDRATE; GLYCERYL LAURATE; CARBOMER 940; GLYCERIN; BUTYROSPERMUM PARKII (SHEA) BUTTER; SIMMONDSIA CHINENSIS (JOJOBA) SEED OIL; WATER

active ingredient

Active Ingredient: Lidocaine 5%
Local Anesthetic

Inactive Ingredients

Inactive Ingredients: Aloe Barbadensis Leaf Extract, Alpha Bisabolol, Benzyl Alcohol, Carbomer 940, EDTA Disodium, Dihydrate
Glycerin, Glyceryl Monolaurate,Specially Denatured Ethy! Alcohol Formula 40 B 200 Proof, Butirospermum Parki (Shea) Butter,Simmondsia Chinensis (Jojoba)Seed Oil, Water, Purified

warning

Storage: Please store in a dry, cool place and out of reach of children

purpose

Efficacy: numb the skin, suitable for tattoos, micro-plastic surgery, permanent makeup.

Indication

Usage: external use on skin

keep out of children

Please store in a dry, cool place and out of reach of children

Dosage

Apply 2 mm to 3 mm of anesthetic cream to the surgical area

when to use

Step instructions:
1. Clean the skin of the surgical area
3.Cover with plastic wrap and wait 45-60 minutes
2. Apply 2 mm to 3 mm of anesthetic cream to the surgical area
4. Wipe off the residue, rinse well, and then start tattooing.

stop to use

Note: if You feel uncomfortable during use, please stop usina it immediately and seek medical treatment if necessary